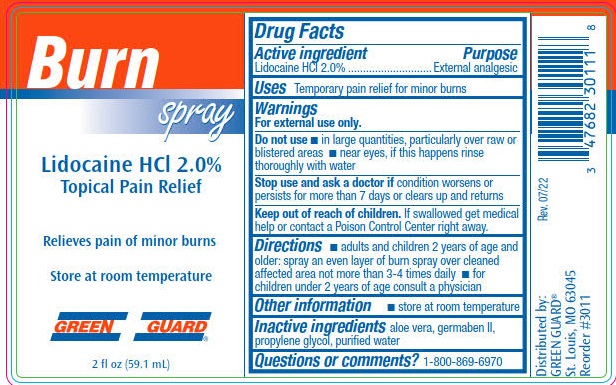 DRUG LABEL: Lidocaine Hydrochloride
NDC: 47682-308 | Form: SPRAY
Manufacturer: Unifirst First Aid Corporation
Category: otc | Type: HUMAN OTC DRUG LABEL
Date: 20250908

ACTIVE INGREDIENTS: LIDOCAINE HYDROCHLORIDE 20 g/1 L
INACTIVE INGREDIENTS: PROPYLPARABEN; METHYLPARABEN; WATER; ALOE VERA LEAF; PROPYLENE GLYCOL; DIAZOLIDINYL UREA

Green Guard Burn Spray

Drug Facts

Active ingredient

Lidocaine HCl 2.0%

Purpose

External analgesic

Uses

Temporary pain relief for minor bums

Warnings

For external use only.

Do not use

- in large quantities, particularly over raw or blistered areas
- near eyes, if this happens rinse thoroughly with water

Stop use and ask a doctor if condition worsens or persists for more than 7 days or clears up and returns.

Keep out of reach of children. If swallowed get medical help or contact a Poison Control Center right away.

Directions

- adults and children 2 years of age and older: spray an even layer of bum spray over cleaned affected area not more than 3-4 times daily
- for children under 2 years of age consult a physician

Other information

- store at room temperature

Inactive ingredients

aloe vera, germaben II, propylene glycol, purified water

Questions or comments? 1-800-634-7680

Green Guard Burn Spray Label

Burn
Spray

Lidocaine HCl 2.0%

Topical Pain Relief

relieves pain of minor burn

Store at room temperature

GREEN GUARD

2 fl oz (59.1 ML)